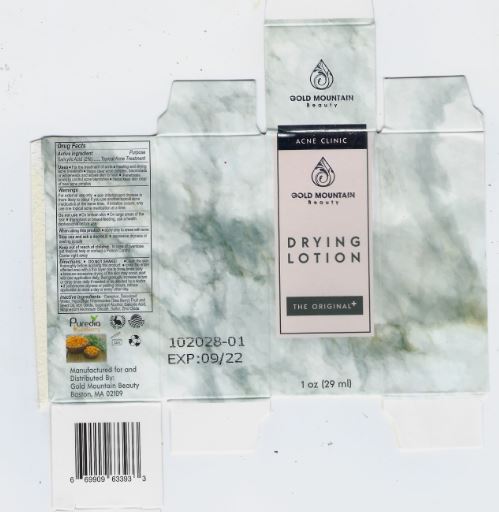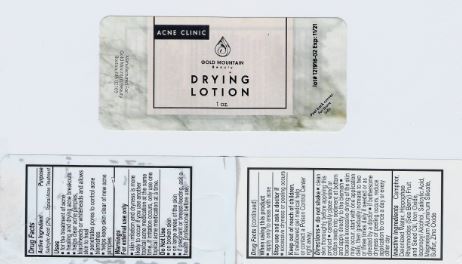 DRUG LABEL: Gold Mountain Beauty Drying
NDC: 76348-461 | Form: SUSPENSION
Manufacturer: RENU LABORATORIES, INC.
Category: otc | Type: HUMAN OTC DRUG LABEL
Date: 20210104

ACTIVE INGREDIENTS: SALICYLIC ACID 0.56 g/29 mL
INACTIVE INGREDIENTS: ISOPROPYL ALCOHOL; WATER; MAGNESIUM ALUMINUM SILICATE; HIPPOPHAE RHAMNOIDES SEED OIL; HIPPOPHAE RHAMNOIDES FRUIT OIL; ZINC OXIDE; FERRIC OXIDE RED; SULFUR; CAMPHOR, (-)-

Gold Mountain Beauty Drying Lotion

ACTIVE INGREDIENT

Salicylic Acid 2 percent

PURPOSE

Topical Acne Treatment

Uses

- for the treatment of acne
- healing and drying acne breakouts
- helps clear acne pimples, blackheads or whiteheads and allows skin to heal
- penetrates pores to control acne blemishes
- helps keep skin clear of new acne pimples

Warnings

For external use only

- skin irritation and dryness is more likely to occur if you use another topical acne medication at the same time. If irritation occurs, only use one topical acne medication at a time.

Do Not Use

- on broken skin
- on large areas of the skin
- if pregnant or breast-feeding, ask a health professional before use.

Directions

- do not shake
- clean skin thoroughly before applying this product
- carefully place wand or cotton swab into sediment at bottom and apply directly to blemish
- because excessive drying of the skin may occur, start with one application daily, then gradually increase to two or three times daily if needed or as directed by a doctor
- if bothersome dryness or peeling occurs, reduce application to once a day or every other day

RECENT MAJOR CHANGES

In Directions only a date was changed

Each section required only a date change

INACTIVE INGREDIENT

Camphor, Deionized Water, Hippophae Rhamnoides (Sea Berry) Fruit and Seed Oil, Iron Oxide, Isopropyl Alcohol, Magnesium Aluminum Silicate, Sulfur, Zinc Oxide

Keep out of reach of children

If swallowed get medical help or contact a Poison Control Center right away

LABEL AND BOX ART FOR DRYING LOTION